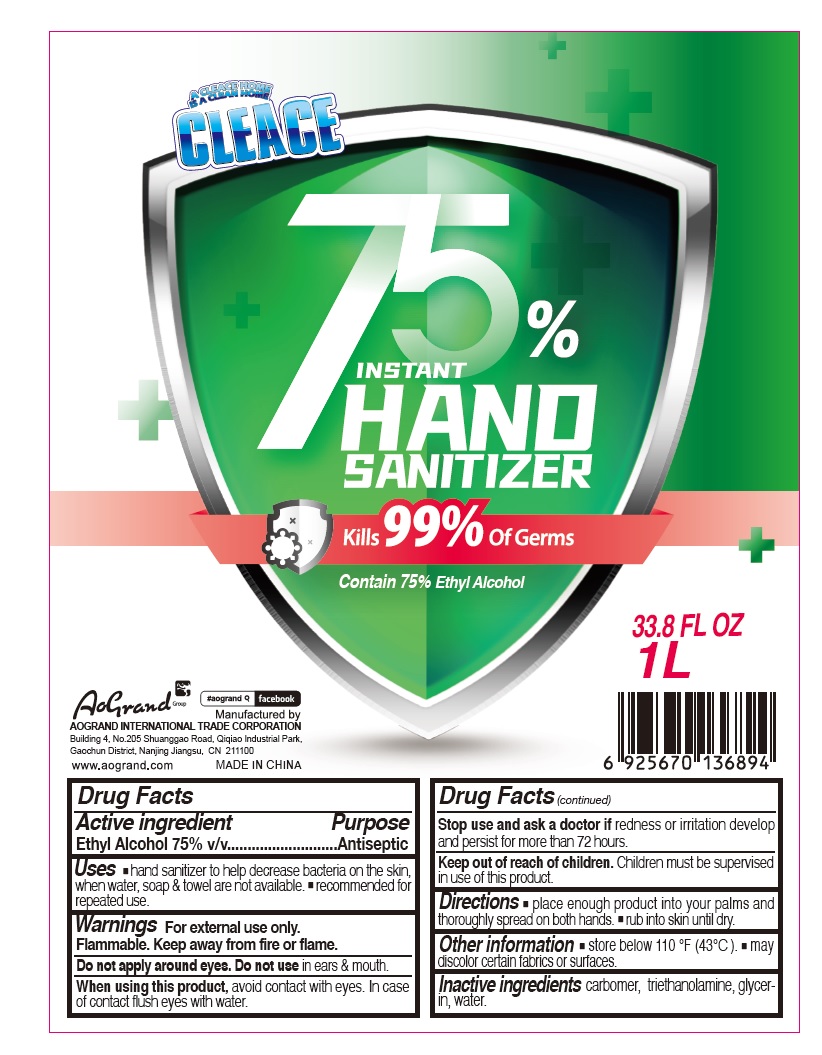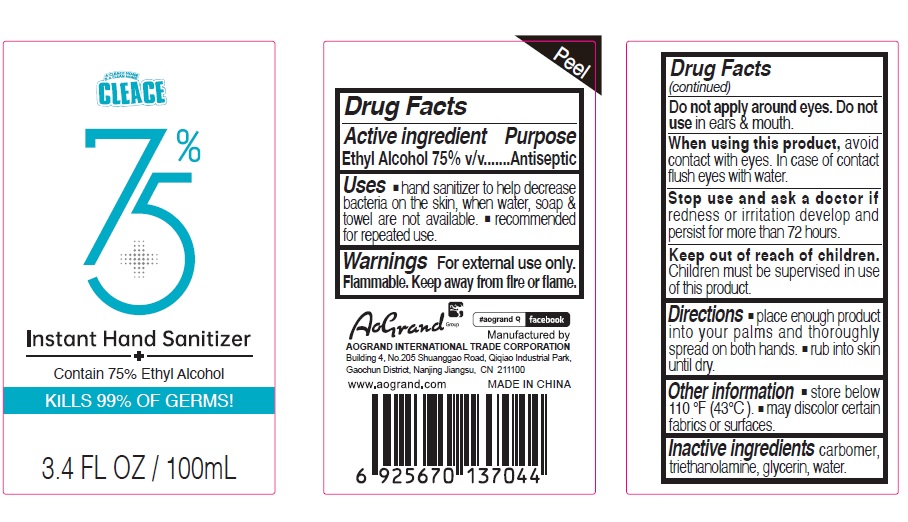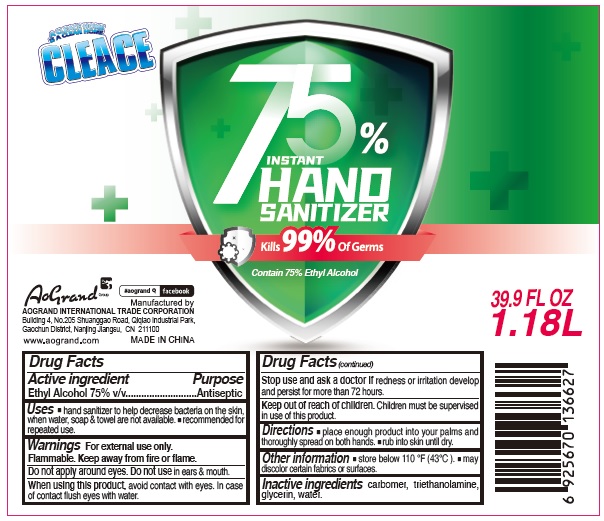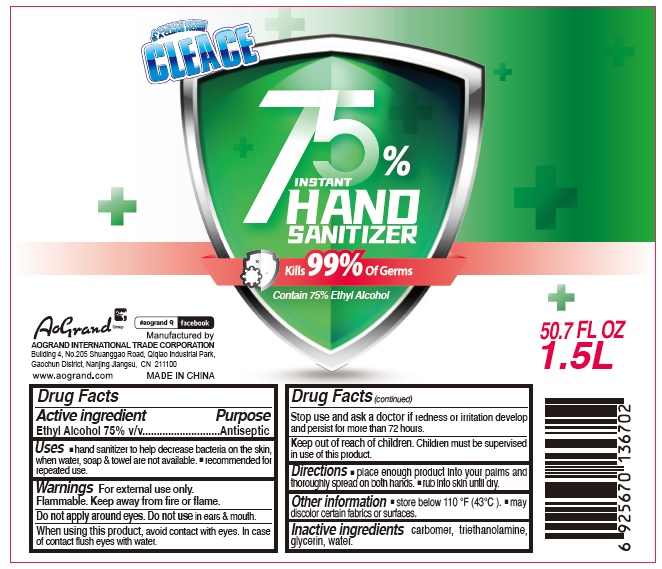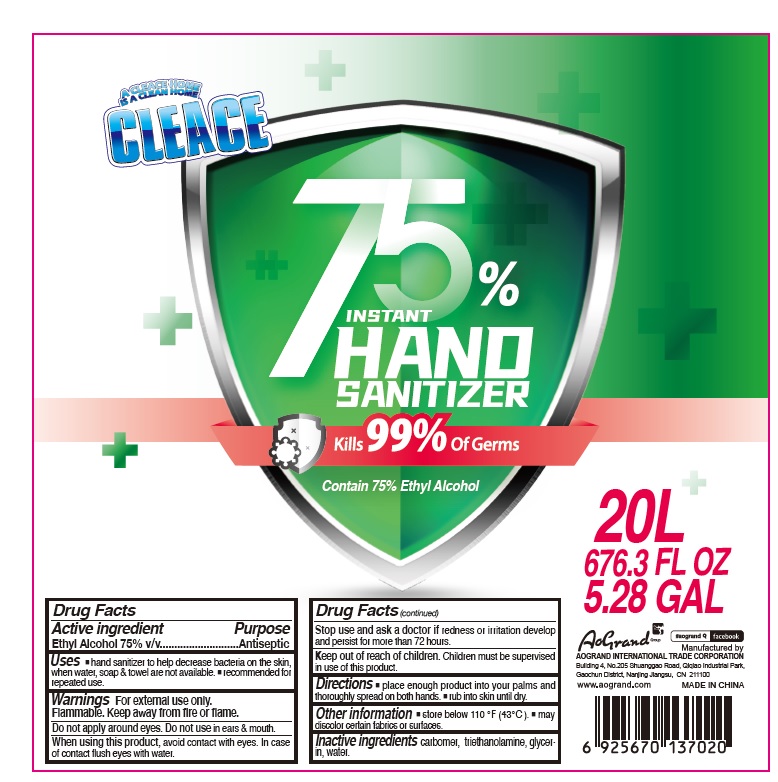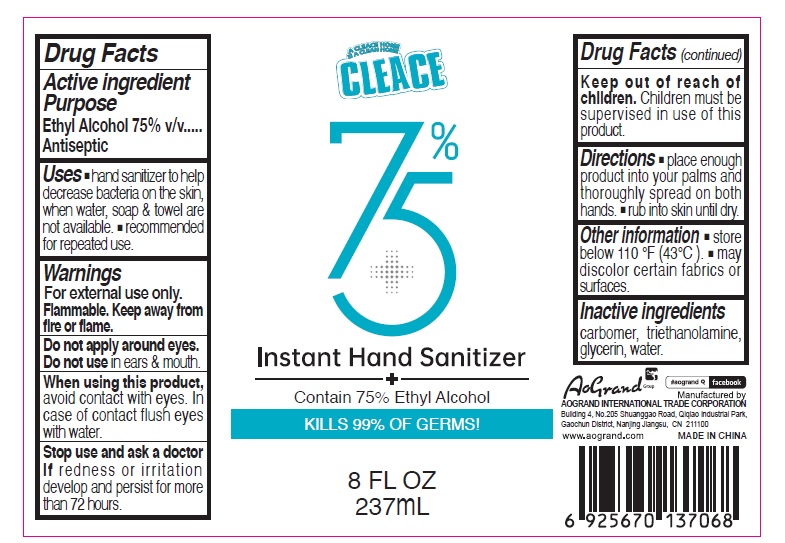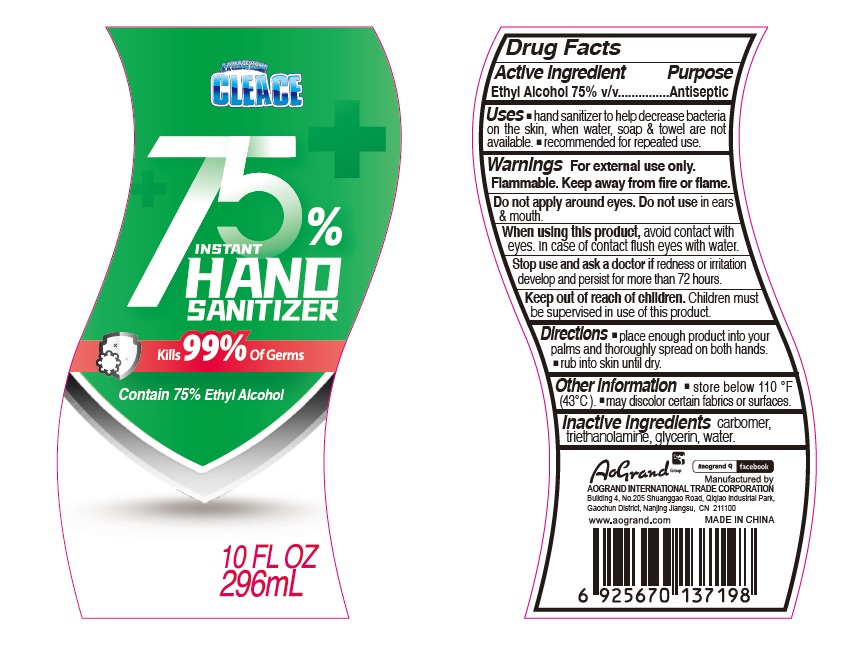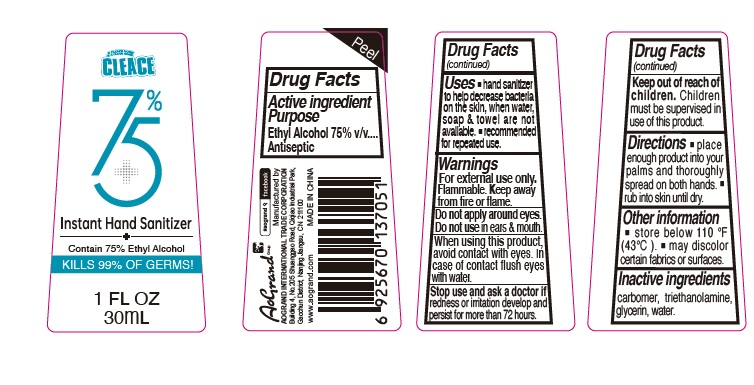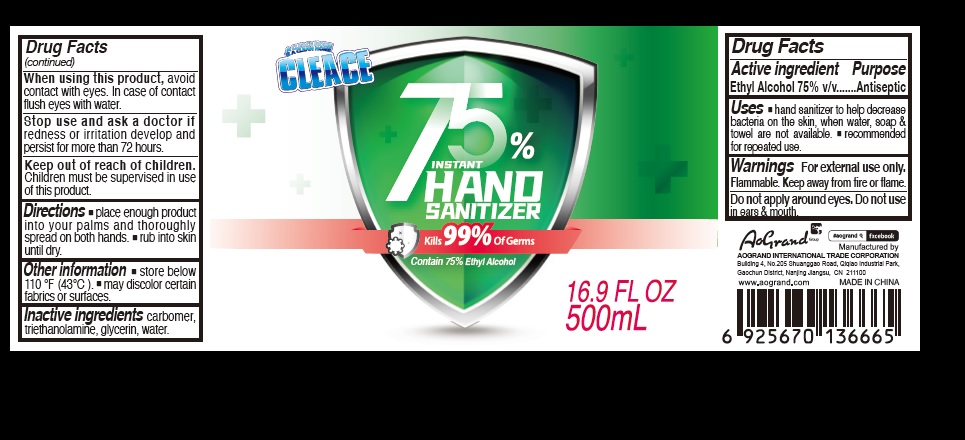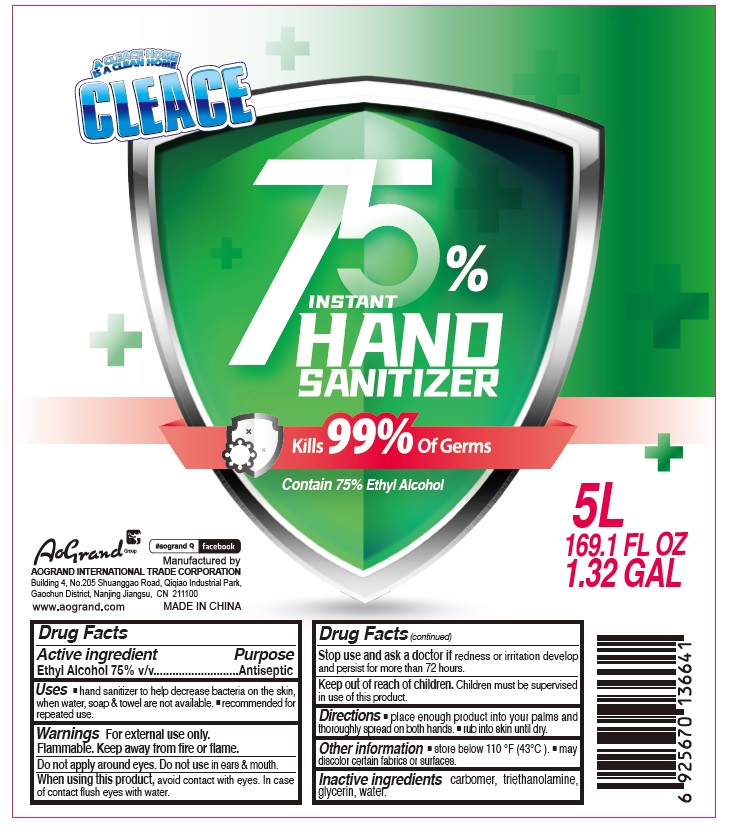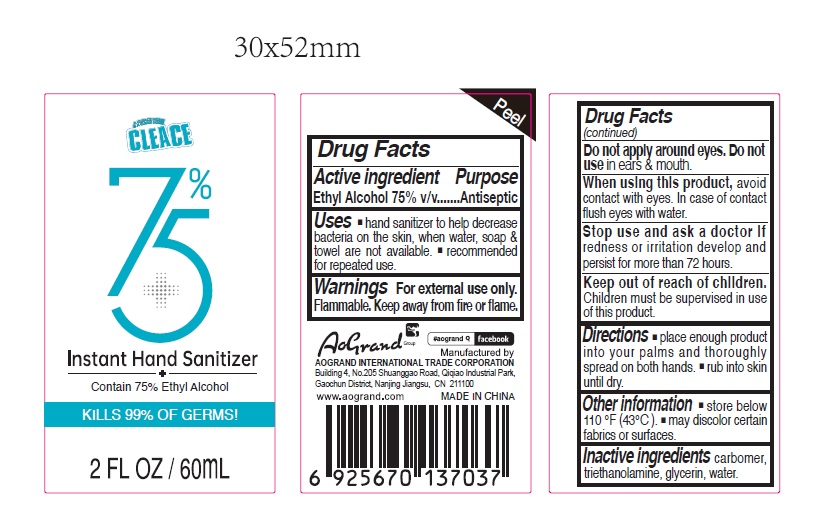 DRUG LABEL: CLEACE
NDC: 74621-002 | Form: GEL
Manufacturer: Nanjing Aogrand Int'l Corp
Category: otc | Type: HUMAN OTC DRUG LABEL
Date: 20200407

ACTIVE INGREDIENTS: ALCOHOL 7.5 mg/1 mL
INACTIVE INGREDIENTS: CARBOMER HOMOPOLYMER, UNSPECIFIED TYPE; TROLAMINE; GLYCERIN; WATER

CLEACE

Active Ingredient

Ethyl Alcohol

Purpose

Antiseptic

Uses

- hand sanitizer to help decrease bacteria on the skin, when water, soap & towel are not available.
- recommended for repeated use.

Warnings

For external use only.

Flammable. Keep away from fire or flame.

Do not apply around eyes. Do not use in ears & mouth.

When using this product, avoid contact with eyes. In case of contact flush eyes with water.

Stop use and ask a doctor if redness or irritation develop and persist for more than 72 hours.

Keep out of reach of children.

Children must be supervised in use of this product.

Directions

- place enough product into your palms and thoroughly spread on both hands.
- rub into skin until dry.

Other information

- store below 110°F (43°C).
- may discolor certain fabrics or surfaces.

Inactive ingredients

carbomer, triethanolamine, glycerin, water